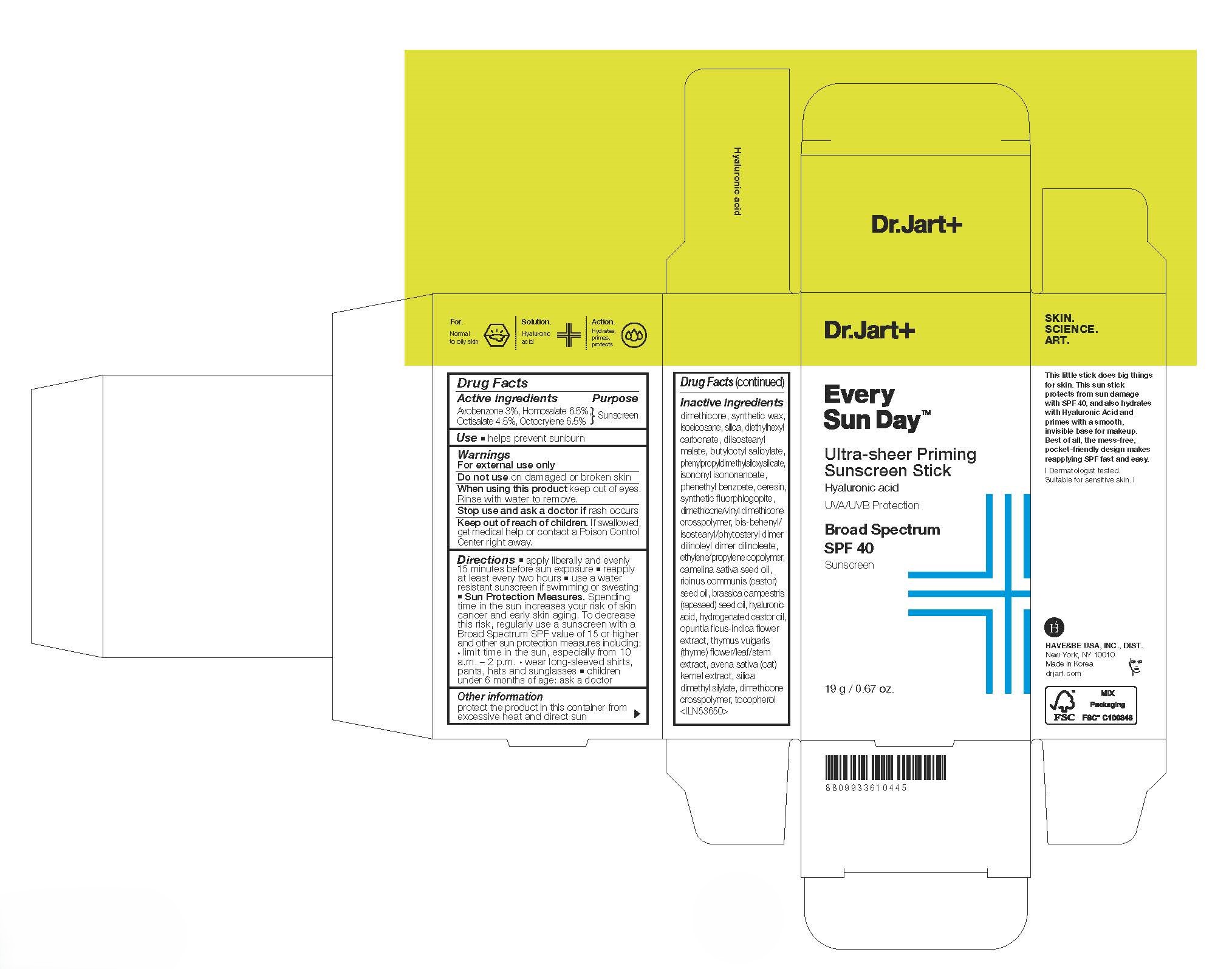 DRUG LABEL: Every Sun Day Ultra-Sheer Priming Sunscreen Stick
NDC: 49404-155 | Form: STICK
Manufacturer: Have & Be Co., Ltd.
Category: otc | Type: HUMAN OTC DRUG LABEL
Date: 20250128

ACTIVE INGREDIENTS: AVOBENZONE 30 mg/1 g; OCTISALATE 45 mg/1 g; OCTOCRYLENE 65 mg/1 g; HOMOSALATE 65 mg/1 g
INACTIVE INGREDIENTS: ISOEICOSANE; DIISOSTEARYL MALATE; PHENETHYL BENZOATE; MAGNESIUM POTASSIUM ALUMINOSILICATE FLUORIDE; BRASSICA CAMPESTRIS (RAPESEED) SEED OIL; OPUNTIA FICUS-INDICA FLOWER; THYME; DIMETHICONE; SILICA; HYALURONIC ACID; DIMETHICONE/VINYL DIMETHICONE CROSSPOLYMER (HARD PARTICLE); ISONONYL ISONONANOATE; RICINUS COMMUNIS (CASTOR) SEED OIL; CAMELINA SATIVA SEED OIL; DIETHYLHEXYL CARBONATE; SILICA DIMETHYL SILYLATE; DIMETHICONE CROSSPOLYMER; TOCOPHEROL; SYNTHETIC WAX (1200 MW); BUTYLOCTYL SALICYLATE; CERESIN; OAT; BIS-BEHENYL/ISOSTEARYL/PHYTOSTERYL DIMER DILINOLEYL DIMER DILINOLEATE; HYDROGENATED CASTOR OIL

Every Sun Day Ultra-sheer Priming Sunscreen Stick

Active ingredients

Avobenzone 3%, Homosalate 6.5%, Octisalate 4.5%, Octocrylene 6.5%

Purpose

Sunscreen

Use

helps prevent sunburn

For external use only

Do not use

on damaged or broken skin

When using this product

keep out of eyes.Rinse with water to remove.

Stop use and ask a doctor if

rash occurs

Keep out of reach of children.

If swallowed, get medical help or contact a Poison Control Center right away.

Directions

For sunscreen use:
apply liberally 15 minutes before sun exposure
reapply at least every two hours
use a water resistant sunscreen if swimming or sweating
Sun Protection Measures. Spending time in the sun increases your risk of skin cancer and early skin aging. To decrease this risk, regularly use a sunscreen with a Broad Spectrum SPF value of 15 or higher and other sun protection measures including:
limit time in the sun, especially from 10 a.m.–2 p.m.
wear long-sleeved shirts, pants, hats and sunglasses
children under 6 months of age: ask a doctor

Inactive ingredients

dimethicone,synthetic wax,isoeicosane,silica,diethylhexyl carbonate,diisostearyl malate,butyloctyl salicylate,phenylpropyldimethylsiloxysilicate,isononyl isononanoate,phenethyl benzoate,ceresin,synthetic fluorphlogopite,dimethicone/vinyl dimethicone crosspolymer,bis-behenyl/isostearyl/phytosteryl dimer dilinoleyl dimer dilinoleate,ethylene/propylene copolymer,camelina sativa seed oil,ricinus communis (castor) seed oil,brassica campestris (rapeseed) seed oil,hyaluronic acid,hydrogenated castor oil,opuntia ficus-indica flower extract,thymus vulgaris (thyme) flower/leaf/stem extract,avena sativa (oat) kernel extract,silica dimethyl silylate,dimethicone crosspolymer,tocopherol

Other information

protect the product in this container from excessive heat and direct sun

PACKAGE LABEL

Every Sun Day

Ultra-sheer Priming Sunscreen Stick

Hyaluronic acid

UVA/UVB Protection

Broad Spectrum SPF 40

Sunscreen

19 g / 0.67 oz